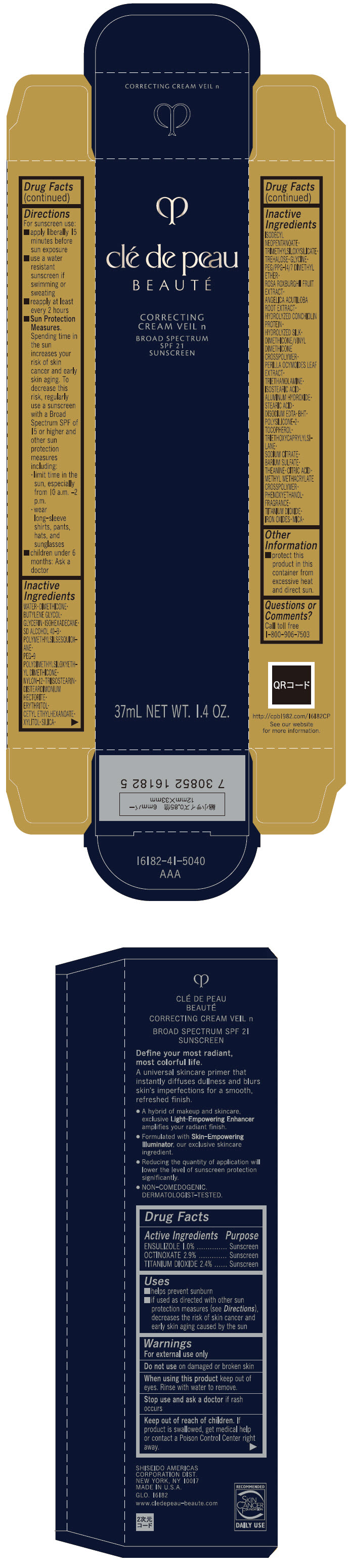 DRUG LABEL: CLE DE PEAU BEAUTE CORRECTING VEIL n
NDC: 58411-483 | Form: CREAM
Manufacturer: SHISEIDO AMERICAS CORPORATION
Category: otc | Type: HUMAN OTC DRUG LABEL
Date: 20260105

ACTIVE INGREDIENTS: ENSULIZOLE 0.386 g/37 mL; OCTINOXATE 1.119 g/37 mL; TITANIUM DIOXIDE 0.9264 g/37 mL
INACTIVE INGREDIENTS: WATER; DIMETHICONE; BUTYLENE GLYCOL; GLYCERIN; ISOHEXADECANE; POLYMETHYLSILSESQUIOXANE (4.5 MICRONS); NYLON-12; TRIISOSTEARIN; DISTEARDIMONIUM HECTORITE; ERYTHRITOL; CETYL ETHYLHEXANOATE; XYLITOL; SILICON DIOXIDE; ISODECYL NEOPENTANOATE; TRIMETHYLSILOXYSILICATE (M/Q 0.6-0.8); TREHALOSE; GLYCINE; PEG/PPG-14/7 DIMETHYL ETHER; ROSA ROXBURGHII FRUIT; ANGELICA ACUTILOBA ROOT; DIMETHICONE/VINYL DIMETHICONE CROSSPOLYMER (SOFT PARTICLE); PERILLA FRUTESCENS LEAF; TROLAMINE; ISOSTEARIC ACID; ALUMINUM HYDROXIDE; STEARIC ACID; EDETATE DISODIUM; BUTYLATED HYDROXYTOLUENE; .ALPHA.-TOCOPHEROL; TRIETHOXYCAPRYLYLSILANE; SODIUM CITRATE, UNSPECIFIED FORM; BARIUM SULFATE; THEANINE; CITRIC ACID MONOHYDRATE; METHYL METHACRYLATE/GLYCOL DIMETHACRYLATE CROSSPOLYMER; PHENOXYETHANOL; FERRIC OXIDE RED; FERRIC OXIDE YELLOW; FERROSOFERRIC OXIDE; MICA

CLÉ DE PEAU BEAUTÉ CORRECTING CREAM VEIL n

Drug Facts

ACTIVE INGREDIENT

Active ingredients | Purpose
Ensulizole 1.0% | Sunscreen
Octinoxate 2.9% | Sunscreen
Titanium Dioxide 2.4 | Sunscreen

Uses

- helps prevent sunburn
- if used as directed with other sun protection measures (see Directions), decreases the risk of skin cancer and early skin aging caused by the sun

Warnings

For external use only

Do not use on damaged or broken skin

WHEN USING

When using this productkeep out of eyes. Rinse with water to remove.

Stop use and ask a doctorif rash occurs.

Keep out of reach of children.If product is swallowed, get medical help or contact a Poison Control Center right away.

Directions

For sunscreen use:

- apply liberally 15 minutes before sun exposure
- use a water resistant sunscreen if swimming or sweating
- reapply at least every 2 hours
- Sun Protection Measures. Spending time in the sun increases your risk of skin cancer and early skin aging. To decrease this risk, regularly use a sunscreen with a broad spectrum SPF of 15 or higher and other sun protection measures including:
  - limit time in the sun, especially from 10 a.m. – 2 p.m.
  - wear long-sleeve shirts, pants, hats, and sunglasses
  - children under 6 months: ask a doctor

Inactive Ingredients

WATER▪DIMETHICONE▪BUTYLENE GLYCOL▪GLYCERIN▪ISOHEXADECANE▪SD ALCOHOL 40-B▪POLYMETHYLSILSESQUIOXANE▪PEG-9 POLYDIMETHYLSILOXYETHYL DIMETHICONE▪NYLON-12▪TRIISOSTEARIN▪DISTEARDIMONIUM HECTORITE▪ERYTHRITOL▪CETYL ETHYLHEXANOATE▪XYLITOL▪SILICA▪ISODECYL NEOPENTANOATE▪TRIMETHYLSILOXYSILICATE▪TREHALOSE▪GLYCINE▪PEG/PPG-14/7 DIMETHYL ETHER▪ROSA ROXBURGHII FRUIT EXTRACT▪ANGELICA ACUTILOBA ROOT EXTRACT▪HYDROLYZED CONCHIOLIN PROTEIN▪HYDROLYZED SILK▪DIMETHICONE/VINYL DIMETHICONE CROSSPOLYMER▪PERILLA OCYMOIDES LEAF EXTRACT▪TRIETHANOLAMINE▪ISOSTEARIC ACID▪ALUMINUM HYDROXIDE▪STEARIC ACID▪DISODIUM EDTA▪BHT▪POLYSILICONE-2▪TOCOPHEROL▪TRIETHOXYCAPRYLYLSILANE▪SODIUM CITRATE▪BARIUM SULFATE▪THEANINE▪CITRIC ACID▪METHYL METHACRYLATE CROSSPOLYMER▪PHENOXYETHANOL▪FRAGRANCE▪TITANIUM DIOXIDE▪IRON OXIDES▪MICA▪

Other information

Protect this product in this container from excessive heat and direct sun.

Questions or comments?

Call toll free 1-800-906-7503

PRINCIPAL DISPLAY PANEL - 37 mL Bottle Carton

clé de peau

BEAUTÉ

CORRECTING
CREAM VEIL n

BROAD SPECTRUM
SPF 21
SUNSCREEN

37mL NET WT. 1.4 OZ.